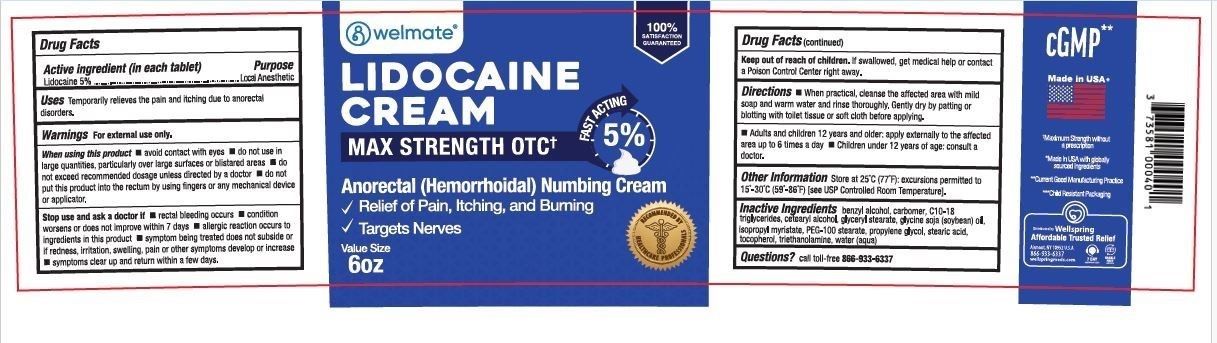 DRUG LABEL: Lidocaine Numbing Cream
NDC: 73581-106 | Form: CREAM
Manufacturer: YYBA Corp
Category: otc | Type: HUMAN OTC DRUG LABEL
Date: 20251103

ACTIVE INGREDIENTS: LIDOCAINE HYDROCHLORIDE ANHYDROUS 5 g/100 mL
INACTIVE INGREDIENTS: CHOLESTEROL; ISOPROPYL MYRISTATE; ALPHA-TOCOPHEROL ACETATE; BENZYL ALCOHOL; LECITHIN, SOYBEAN; TROLAMINE; PROPYLENE GLYCOL; WATER; POLYSORBATE 80; CARBOMER 940

NIV40- Lidocaine Numbing Cream

Active Ingredient

Lidocaine 5%

Purpose

External Analgesic

When using this product

Avoid contact with eyes. Do not use in large quantities, particularly over large surfaces or blistared areas. Do no exceed recommended dosage unless directed by a doctor. Do not put this product into the rectum by using fingers or any mechanical device or applicator

Stop use and ask a doctor if

rectal bleeding occurs. condition worsens or does not improve within 7 days. allergic reaction occurs to ingredients in this product. symptom being treated does not subside or if redness, irritation, swelling, pain or other symptoms develop or increase. symptoms clear up and return within a few days

Keep out of reach of children

If swallowed, get medical help or contact a Poison Control Center right away

Questions

call toll free 866-933-6337

WARNINGS

For external use only

INACTIVE INGREDIENT

Inactive Ingredients: Benzyl alcohol, carbomer, C10-18 triglycerides, cetearyl alcohol, glycel stearate, glycine soja (soybean) oil, isopropyl myristate, PEG-100 stearate, propylene glycol, stearic acid, tocopherol, triethanolamine, water (aqua)

Uses

Temporarily relieves the pain and itching due to anorectal disorders.

DOSAGE AND ADMINISTRATION

Local anesthetic